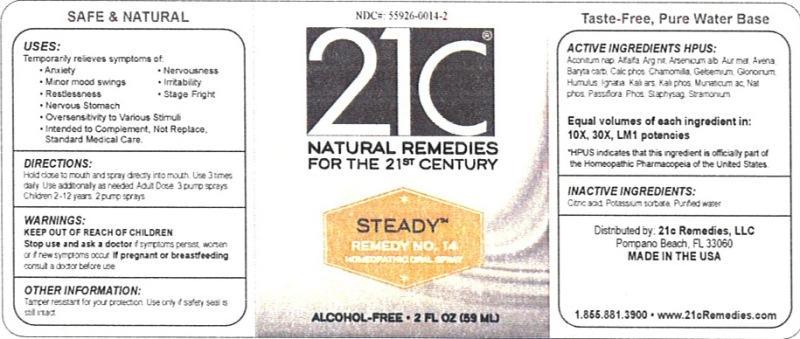 DRUG LABEL: Steady Remedy No. 14
NDC: 55926-0014 | Form: LIQUID
Manufacturer: Speer Laboratories, LLC
Category: homeopathic | Type: HUMAN OTC DRUG LABEL
Date: 20130731

ACTIVE INGREDIENTS: ACONITUM NAPELLUS 10 [hp_X]/59 mL; ALFALFA 10 [hp_X]/59 mL; SILVER NITRATE 10 [hp_X]/59 mL; ARSENIC TRIOXIDE 10 [hp_X]/59 mL; GOLD 10 [hp_X]/59 mL; AVENA SATIVA FLOWERING TOP 10 [hp_X]/59 mL; BARIUM CARBONATE 10 [hp_X]/59 mL; TRIBASIC CALCIUM PHOSPHATE 10 [hp_X]/59 mL; MATRICARIA RECUTITA 10 [hp_X]/59 mL; GELSEMIUM SEMPERVIRENS ROOT 10 [hp_X]/59 mL; NITROGLYCERIN 10 [hp_X]/59 mL; HOPS 10 [hp_X]/59 mL; STRYCHNOS IGNATII SEED 10 [hp_X]/59 mL; POTASSIUM ARSENITE ANHYDROUS 10 [hp_X]/59 mL; POTASSIUM PHOSPHATE, DIBASIC 10 [hp_X]/59 mL; HYDROCHLORIC ACID 10 [hp_X]/59 mL; SODIUM PHOSPHATE, DIBASIC, HEPTAHYDRATE 10 [hp_X]/59 mL; PASSIFLORA INCARNATA FLOWERING TOP 10 [hp_X]/59 mL; PHOSPHORUS 10 [hp_X]/59 mL; DELPHINIUM STAPHISAGRIA SEED 10 [hp_X]/59 mL; DATURA STRAMONIUM 10 [hp_X]/59 mL
INACTIVE INGREDIENTS: CITRIC ACID MONOHYDRATE; POTASSIUM SORBATE; WATER

Steady Remedy No. 14

Active Ingredient HPUS: Aconitum napellus, Alfalfa, Argentum nitricum, Arsenicum album, Aurum metallicum, Avena sativa, Baryta carbonica, Calcarea phosphorica, Chamomilla, Gelsemium sempervirens, Glonoinum, Humulus lupulus, Ignatia amara, Kali arsenicosum, Kali phosphoricum, Muriaticum acidum, Natrum phosphoricum, Passiflora incarnata, Phosphorus, Staphysagria, Stramonium.

Equal volumes of each ingredient in: 10X, 30X, LM1 potencies.

HPUS indicates that this ingredient is officially part of the Homeopathic Pharmacopia of the United States.

Inactive Ingredients: Citric acid, Potassium sorbate, Purified water.

INDICATIONS AND USAGE

Uses: Temporarily relieves symptoms of:

- anxiety
- minor mood swings
- restlessness
- nervous stomach
- nervousness
- irritability
- stage fright
- oversensitivity to various stimuli
- intended to complement, not replace, standard medical care.

DOSAGE AND ADMINISTRATION

Directions: Hold close to mouth and spray directly into mouth. Use 3 times daily. Use additionally as needed. Adult Dose: 3 pump sprays. Children 2-12 years: 2 pump sprays.

Keep out of reach of children.

Warnings:

Stop use and ask a doctor if symptoms persist, worsen or if new symptoms occur. If pregnant or breastfeeding, consult a doctor before use.

Other Information: Tamper resistant for your protection. Use only if safety seal is still intact.

PURPOSE

Uses: Temporarily relieves symptoms of: anxiety, minor mood swings, restlessness, nervous stomach, nervousness, irritability, stage fright,

oversensitivity to various stimuli, intended to complement, not replace, standard medical care.